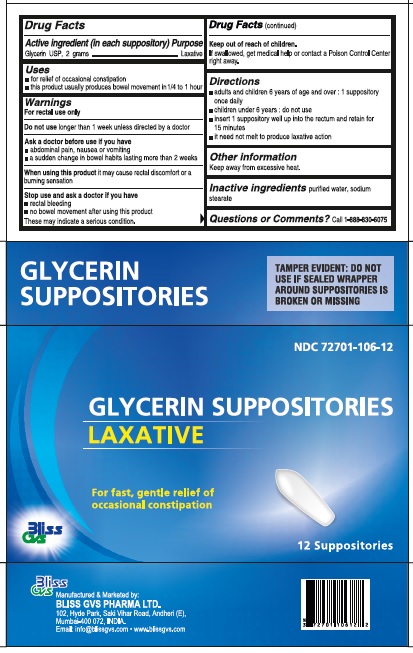 DRUG LABEL: Bliss GVS
NDC: 72701-106 | Form: SUPPOSITORY
Manufacturer: Bliss GVS Pharma Limited
Category: otc | Type: HUMAN OTC DRUG LABEL
Date: 20241010

ACTIVE INGREDIENTS: GLYCERIN 2 g/1 1
INACTIVE INGREDIENTS: WATER; SODIUM STEARATE

Glycerin Suppositories

Drug Facts

Active ingredient

Glycerin USP, 2 grams

Purpose

Laxative

Uses

- for relief of occasional constipation
- this product usually produces bowel movement in 1/4 to 1 hour

Warnings

For rectal use only

DO NOT USE

Do not uselonger than 1 week unless directed by a doctor

Ask a doctor before use if you have

- abdominal pain, nausea or vomiting
- a sudden change in bowel habits lasting more than 2 weeks

WHEN USING

When using this productit may cause rectal discomfort or a burning sensation

Stop use and ask a doctor if you have

- rectal bleeding
- no bowel movement after using this product

These may indicate a serious condition.

Keep out of reach of children.If swallowed, get medical help or contact a Poison Control Center right away.

Directions

- adults and children 6 years and over: 1 suppository once daily
- children under 6 years: do not use
- insert 1 suppository well up into rectum and retain for 15 minutes
- it need not melt to produce laxative action

Other information

keep away from excessive heat

Inactive ingredientspurified water, sodium stearate

Questions or Comments?Call 1-888-830-6075

TAMPER EVIDENT: DO NOT USE IF SEALED WRAPPER AROUND SUPPOSITORIES IS BROKEN OR MISSING

Manufactured and Marketed by:

BLISS GVS PHARMA LTD.

102, Hyde Park, Saki Vihar Road, Andheri(E),

Mumbai-400 072, INDIA

Email: info@blissgvs.com • www.blissgvs.com

PACKAGE LABEL

NDC 72701-106-12

GLYCERIN SUPPOSITORIES

LAXATIVE

For fast, gentle relief of occasional constipation

12 Suppositories